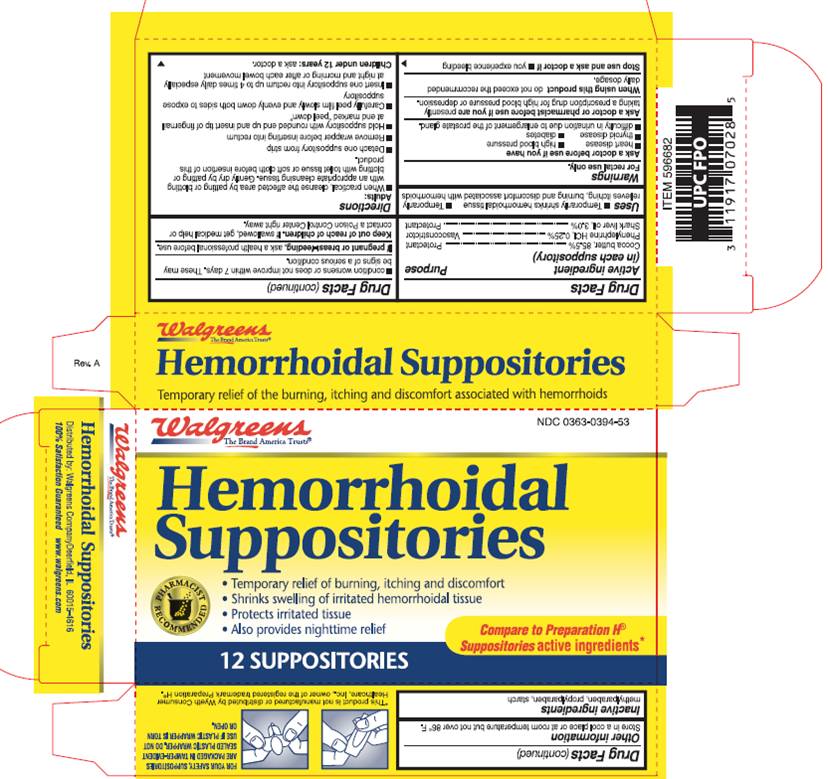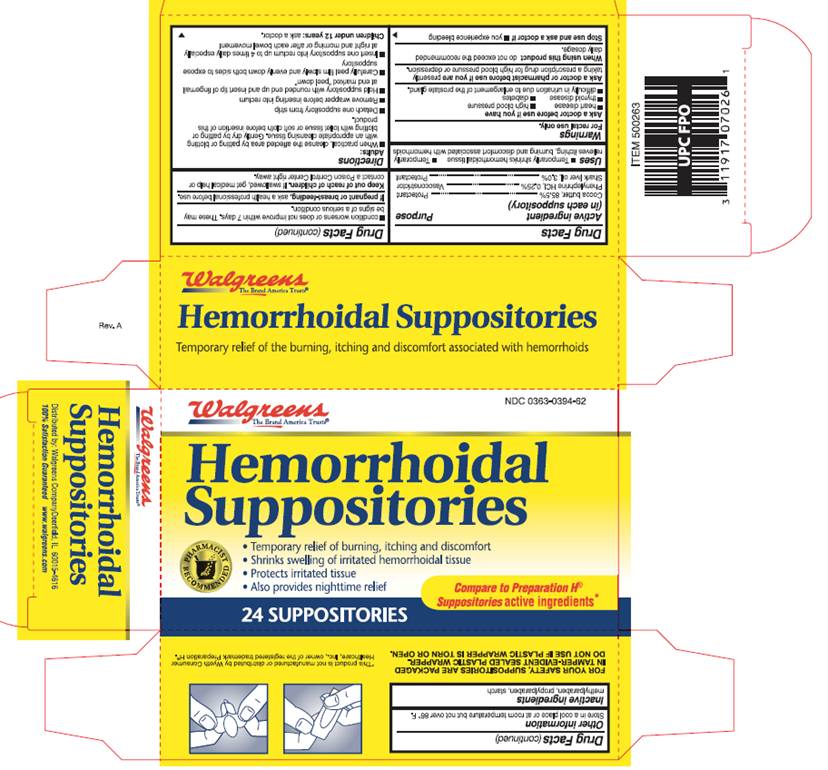 DRUG LABEL: phenylephrine hydrochloride
NDC: 0363-0394 | Form: SUPPOSITORY
Manufacturer: Walgreen Company
Category: otc | Type: HUMAN OTC DRUG LABEL
Date: 20100201

ACTIVE INGREDIENTS: cocoa butter 2077 mg/1 1; phenylephrine hydrochloride 6 mg/1 1; shark liver oil 73 mg/1 1
INACTIVE INGREDIENTS: methylparaben; propylparaben; starch, corn

DRUG FACTS

ACTIVE INGREDIENTS

Cocoa butter, 85.5%
Phenylephrine HCI, 0.25%
Shark liver oil, 3.0%

PURPOSE

protectant

vasoconstrictor

protectant

USES

- Temporarily shrinks hemorrhoidal tissue
- Temporarily relieves itching burning and discomfort associated with hemorrhoids

WARNINGS

For rectal use only.

Ask a doctor before use if you have

- heart disease
- thyroid disease
- difficulty in urination due to enlargement of the prostate gland
- high blood pressure
- diabetes

Ask a doctor or pharmacist before use if you are

presently taking a prescription drug for high blood pressure or depression.

When using this product

do not exceed the recommended daily dosage.

Stop use and ask a doctor if

- you experience bleeding
- condition worsens or does not improve within 7 days.

These may be signs of a serious condition.

If pregnant or breastfeeding

ask a health professional before use.

Keep out of reach of children

If swallowed, get medical help or contact a Poison Control Center right away.

DIRECTIONS

Adults:

- When practical, cleanse the affected area by patting or blotting with an appropriate cleansing tissue. Gently dry by patting or blotting with toilet tissue or soft cloth before insertion of this product.
- Detach one suppository from strip
- Remove wrapper before inserting into rectum
- Hold suppository with rounded end up and insert tip of fingernail at end marked "peel down"
- Carefully peel film slowly and evenly down both sides to expose suppository
- Insert one suppository into rectum up to 4 times daily especially at night and morning or after each bowel movement

Children under 12 years: ask a doctor

STORAGE

Store in a cool place or at room temperature but not over 86° F.

INACTIVE INGREDIENTS

methylparaben, propylparaben, starch

BOX INFORMATION - 12 count

Walgreens

NDC 0363-0394-53

Hemorrhoidal
Suppositories

- Temporary relief of burning, itching and discomfort
- Shrinks swelling of irritated hemorrhoidal tissue
- Protects irritated tissue
- Also provides nighttime relief

Compare to Preparation H Suppositories® active ingredients*
12 SUPPOSITORIES
FOR YOUR SAFETY, SUPPOSITORIES ARE PACKAGED IN TAMPER-EVIDENT SEALED PLASTIC WRAPPER. DO NOT USE IF PLASTIC WRAPPER IS TORN OR OPEN.
*This product is not manufactured or distributed by Wyeth Consumer Healthcare, Inc., owner of the registered trademark Preparation H®.
Distributed by Walgreens Company, Deerfield, IL 60015-4616
100% Satisfaction Guaranteed www.walgreens.com

BOX INFORMATION - 24 count

Walgreens
NDC 0363-0394-62
Hemorrhoidal
Suppositories

- Temporary relief of burning, itching and discomfort
- Shrinks swelling of irritated hemorrhoidal tissue
- Protects irritated tissue
- Also provides nighttime relief

Compare to Preparation H Suppositories® active ingredients*
24 SUPPOSITORIES
FOR YOUR SAFETY, SUPPOSITORIES ARE PACKAGED IN TAMPER-EVIDENT SEALED PLASTIC WRAPPER. DO NOT USE IF PLASTIC WRAPPER IS TORN OR OPEN.
*This product is not manufactured or distributed by Wyeth Consumer Healthcare, Inc., owner of the registered trademark Preparation H®.
Distributed by Walgreens Company, Deerfield, IL 60015-4616
100% Satisfaction Guaranteed www.walgreens.com